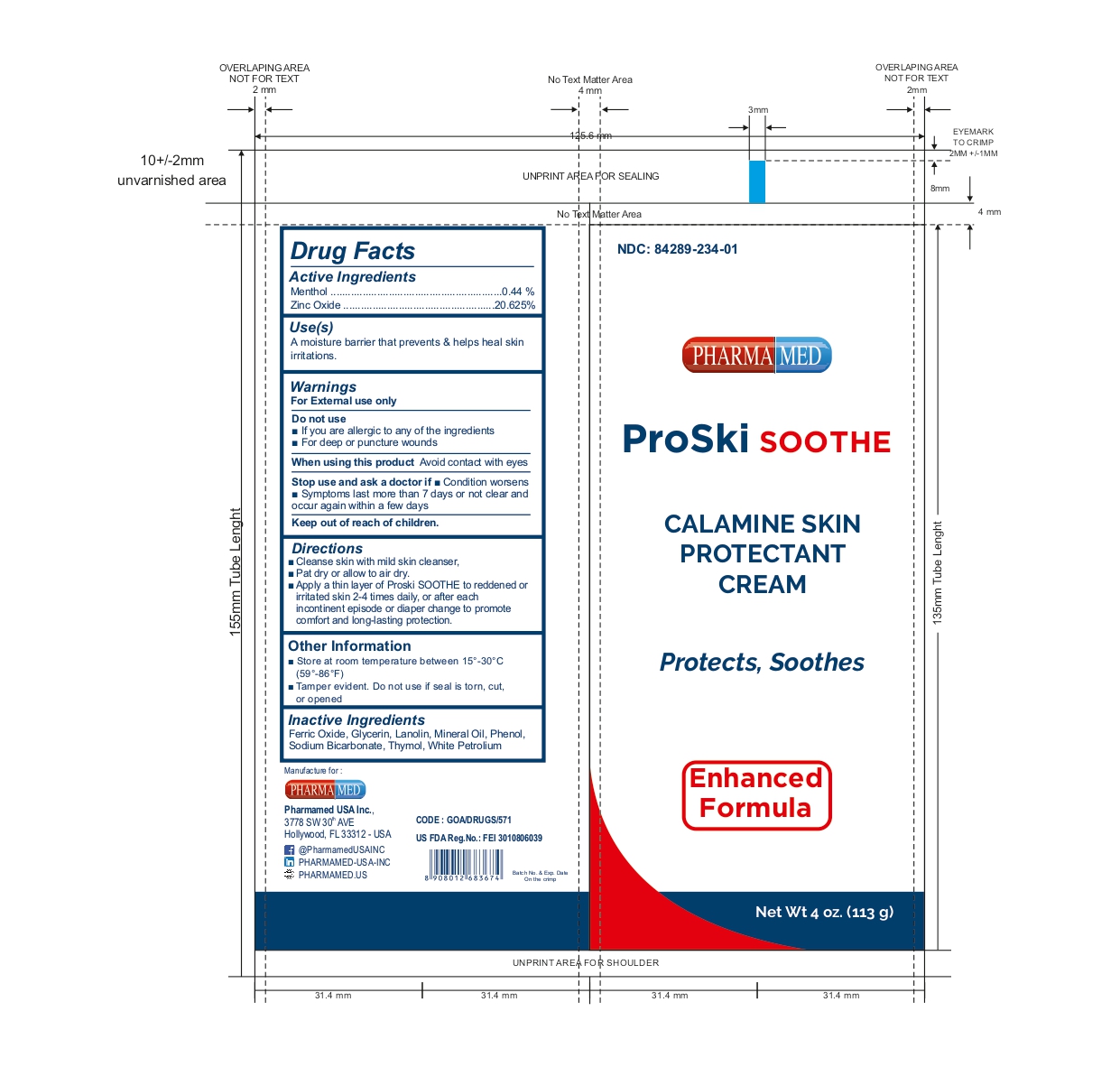 DRUG LABEL: PROSKI SOOTHE
NDC: 84289-234 | Form: CREAM
Manufacturer: PHARMAMED USA INC
Category: otc | Type: HUMAN OTC DRUG LABEL
Date: 20250318

ACTIVE INGREDIENTS: ZINC OXIDE 21 g/100 g; MENTHOL 0.44 g/100 g
INACTIVE INGREDIENTS: PHENOL; GLYCERIN; THYMOL; WHITE PETROLATUM; SODIUM BICARBONATE; MINERAL OIL; LANOLIN; FERRIC OXIDE RED

CALAMINE SKIN PROTECTANT CREAM

ACTIVE INGREDIENT

Menthol 0.44%

Zinc Oxide 20.625%

INDICATION

External Analgesic

Skin Protectant

USE

A moisture barrier that prevents and helps heal skin irritations from:

• Urine • Diarrhea • Perspiration • Fistula drainage • Feeding tube site leakage • Wound drainage (peri-wound skin) • Minor burns • Cuts • Scrapes • Itching

WARNINGS

For external use only

Do not use

• On deep or puncture wounds

When using this product

• Avoid contact with eyes

Stop use and ask a doctor if

• Condition worsens • Symptoms last more than 7 days or clear up and occur again within a few days

Keep out of reach of children

If swallowed, get medical help or contact a Poison Control Center (1-800-222-1222) right away.

DIRECTIONS

• Cleanse skin with mild skin cleanser.

• Pat dry or allow to air dry.

• Apply a thin layer of PROSKI SOOTHE to reddened or irritated skin 2-4 times daily, or after each incontinent episode or diaper change to promote comfort and long-lasting protection.

OTHER INFORMATION

• Store at room temperature 15º-30º C (59º-86º F)

• Tamper evident. Do not use if packet is torn or cut. Do not use if seal is damaged.

INACTIVE INGREDIENTS

Ferric Oxide Red, Glycerin, Lanolin, Mineral Oil, Phenol, Sodium Bicarbonate, Thymol, White Petrolatum

QUESTIONS OR COMMENTS?

(754)-200-8994 (Mon-Fri 8 AM to 4 PM EST)

PACKAGE/LABEL PRINCIPAL DISPLAY PANEL

NDC: 84289-234-01

CALAMINE SKIN PROTECTANT CREAM

Protects, Soothes

Enhanced Formula

Net Wt 4 oz. (113 g)

GOA/DRUGS/571